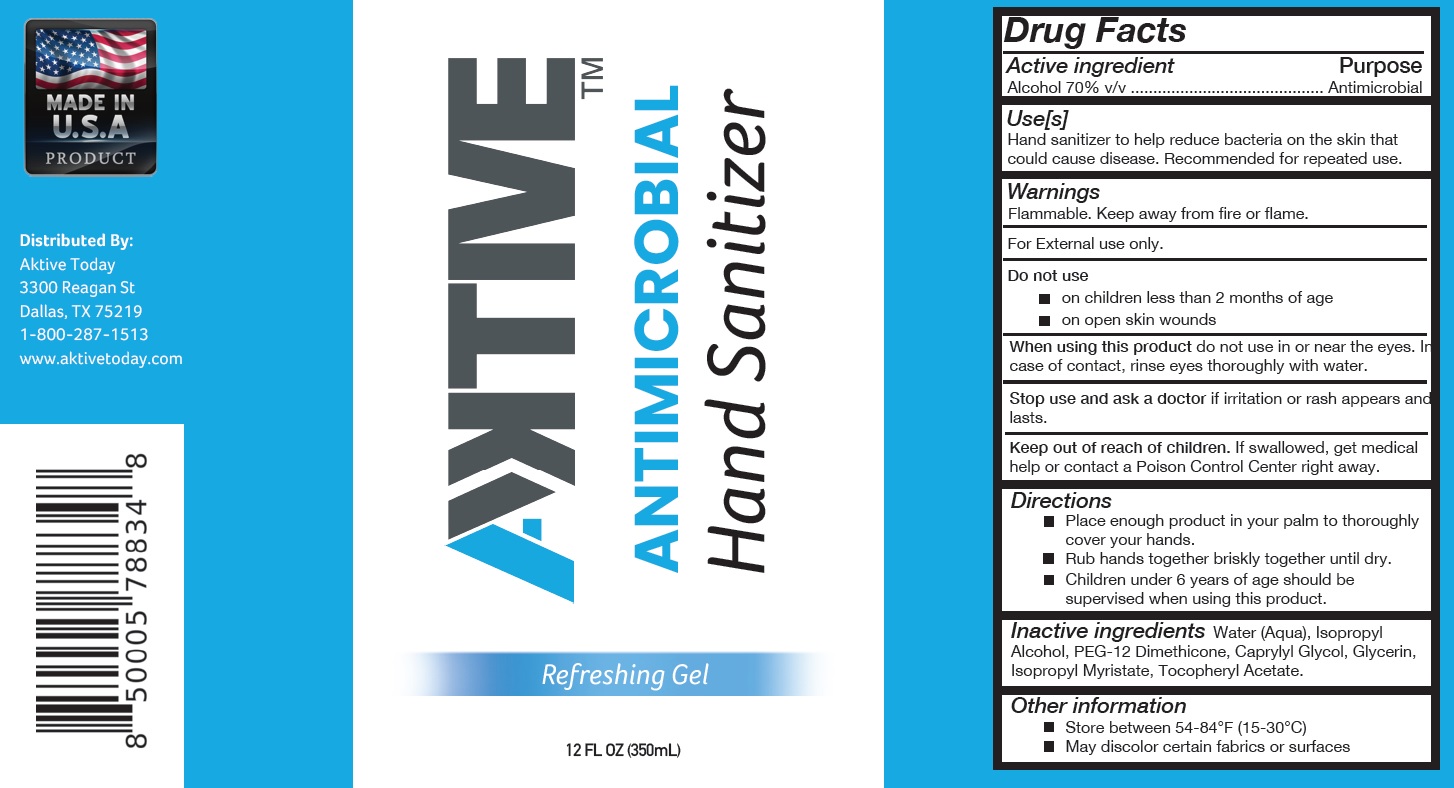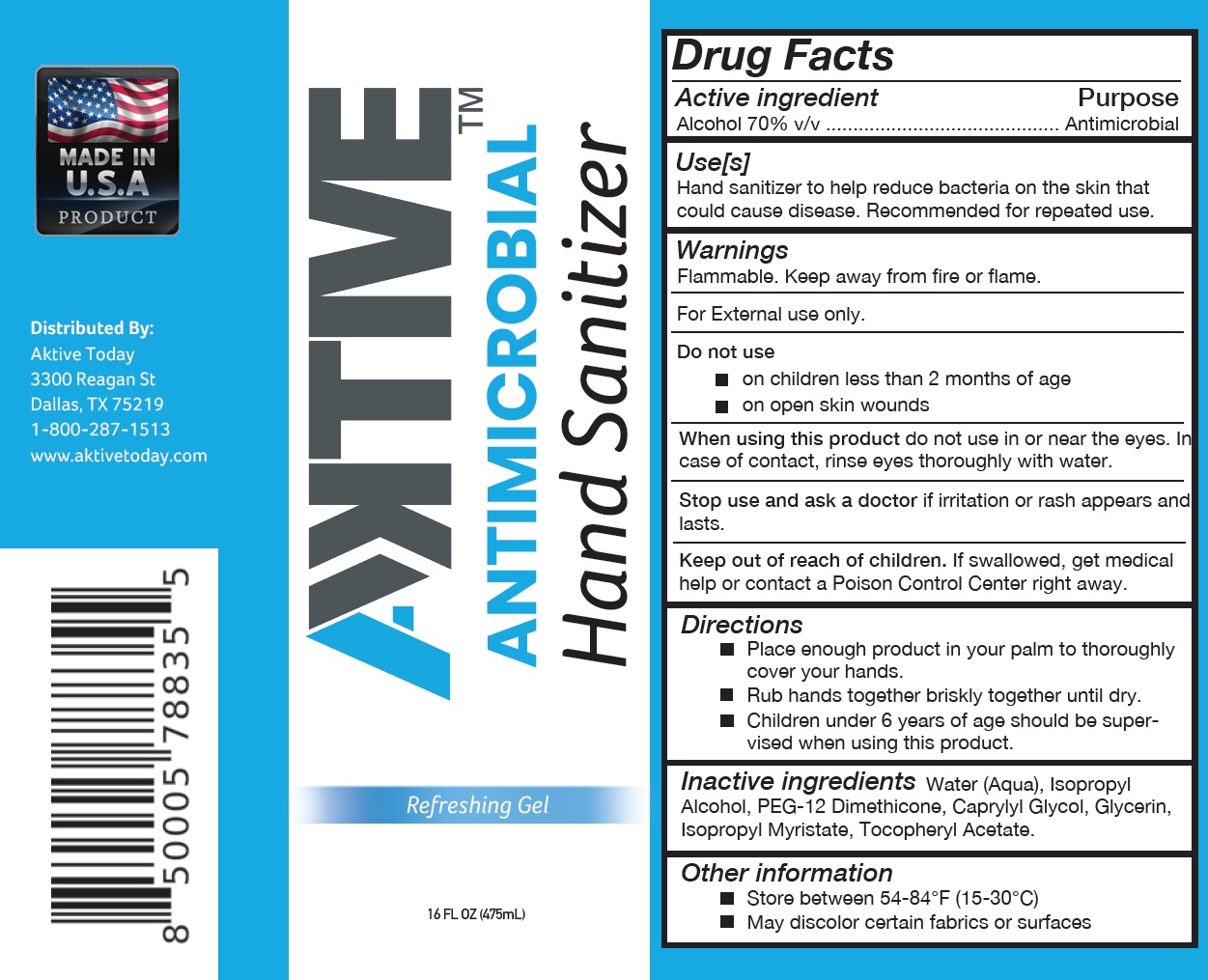 DRUG LABEL: Antimicrobial Hand Sanitizer
NDC: 76939-555 | Form: GEL
Manufacturer: NVIP LLC
Category: otc | Type: HUMAN OTC DRUG LABEL
Date: 20200820

ACTIVE INGREDIENTS: ALCOHOL 0.7 mL/1 mL
INACTIVE INGREDIENTS: WATER; ISOPROPYL ALCOHOL; PEG-12 DIMETHICONE; CAPRYLYL GLYCOL; GLYCERIN; ISOPROPYL MYRISTATE; .ALPHA.-TOCOPHEROL ACETATE

Antimicrobial Hand Sanitizer

Active ingredient

Alcohol 70% v/v

Purpose

Antimicrobial

Use[s]

Hand sanitizer to help reduce bacteria on the skin that could cause disease. Recommended for repeated use.

Warnings

Flammable. Keep away from fire or flame.

For External use only.

Do not use

- on children less than 2 months of age
- on open skin wounds

When using this product

do not use in or near the eyes. In case of contact, rinse eyes thoroughly with water.

Stop use and ask a doctor

if irritation or rash appears and lasts.

Keep out of reach of children.

If swallowed, get medical help or contact a Poison Control Center right away.

Directions

- Place enough product in your palm to thoroughly cover your hands.
- Rub hands together briskly together until dry.
- Children under 6 years of age should be supervised when using this product.

Inactive ingredients

Water (Aqua), Isopropyl Alcohol, PEG-12 Dimethicone, Caprylyl Glycol, Glycerin, Isopropyl Myristate, Tocopheryl Acetate.

Other information

- Store between 54-84°F (15-30°C)
- May discolor certain fabrics or surfaces